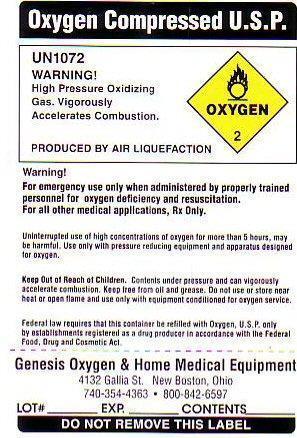 DRUG LABEL: OXYGEN 
NDC: 52481-2481 | Form: GAS
Manufacturer: Genesis Respiratory Services
Category: prescription | Type: HUMAN PRESCRIPTION DRUG LABEL
Date: 20251223

ACTIVE INGREDIENTS: OXYGEN 99.9 L/100 L

PRODUCT WARNINGS AND PRECAUTIONS

KEEP OUT OF REACH OF CHILDREN. CONTENTS UNDER PRESSURE AND CAN VIGOROUSLY ACCELERATE COMBUSTION. KEEP FREE FROM OIL AND GREASE. DON NOT USE OR STORE NEAR HEAT OR OPEN FLAME AND USE ONLY WITH EQUIPMENT CONDITIONED FOR OXYGEN SERVICE.

FEDERAL LAW REQUIRES THAT THIS CONTAINER BE REFILLED WITH OXYGEN U.S.P. ONLY BY ESTABLISHMENTS REGISTERED AS A DRUG PRODUCER IN ACCORDANCE WITH THE FEDERAL FOOD, DRUG, AND COSMETIC ACT.

WARNING: FOR EMERGENCY USE ONLY WHEN ADMINISTERED BY PROPERLY TRAINED PERSONNEL FOR OXYGEN DEFICIENCY AND RESUSCITATION. FOR ALL OTHER MEDICAL APPLICATIONS, Rx ONLY.

UN INTERRUPTED USE OF HIGH CONCENTRATIONS OF OXYGEN FOR MORE THAN 5 HOURS MAY BE HARMFUL. USE ONLY WITH PRESSURE REDUCING EQUIPMENT AND APPARATUS DESIGNED FOR OXYGEN.

LOT# __________ WT. _____________ CONTENTS_________________

OXYGEN COMPRESSED LABEL

OXYGEN COMPRESSED U.S.P. UN 1072 OXYGEN-2

WARNING HIGH PRESSURE OXIDIZING GAS. VIGOROUSLY ACCELERATES COMBUSTION PRODUCED BY AIR LIQUEFACTION

DO NOT REMOVE THIS PRODUCT LABEL